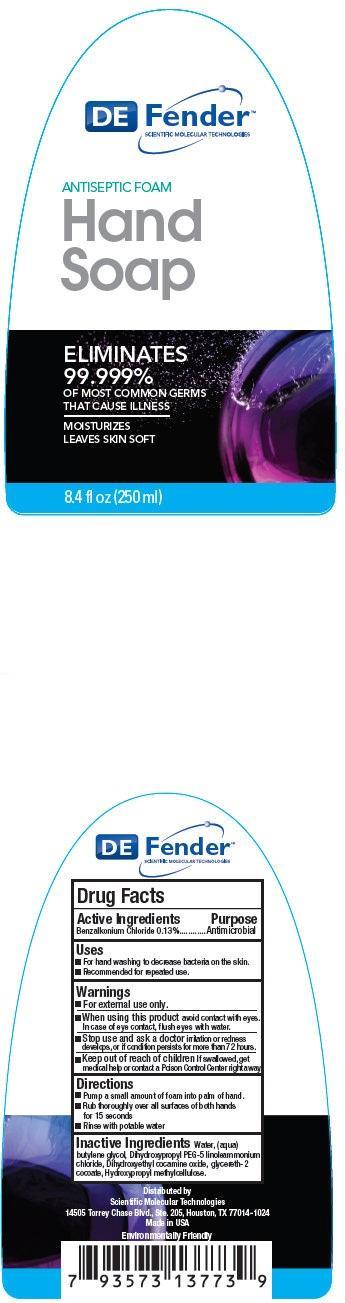 DRUG LABEL: DEFENDER Antiseptic Foam Hand
NDC: 42953-000 | Form: SOAP
Manufacturer: Scientific Molecular Technologies
Category: otc | Type: HUMAN OTC DRUG LABEL
Date: 20210601

ACTIVE INGREDIENTS: BENZALKONIUM CHLORIDE 1.3 mg/1 mL
INACTIVE INGREDIENTS: WATER; BUTYLENE GLYCOL; DIHYDROXYPROPYL PEG-5 LINOLEAMMONIUM CHLORIDE; DIHYDROXYETHYL COCAMINE OXIDE; GLYCERETH-2 COCOATE

DEFENDER Antiseptic Foam Hand

Active Ingredients

Benzalkonium Chloride 0.13%

Purpose

Antimicrobial

Uses

- For hand washing to decrease bacteria on the skin.
- Recommended for repeated use.

Warnings

- For external use only.

When using this product

avoid contact with eyes. In case of eye contact, flush eyes with water.

Stop use and ask a doctor

irritation or redness develops. If condition persists for more than 72 hours.

Keep out of reach of children

If swallowed, get medical help or contact a Poison Control Center right away.

Directions

- Pump a small amount of foam into palm of hand.
- Run thoroughly over all surfaces of both hands for 15 seconds
- Rinse with potable water.

Inactive Ingredients

Water, (aqua), butylene glycol, Dihydroxypropyl PEG-5 linoleammonium chloride, Dihydroxyethyl cocamine oxide, glycereth-2 cocoate, Hydroxypropyl methylcellulose.

PACKAGE LABEL

DE Fender SCIENTIFIC MOLECULAR TECHNOLOGIES ANTISEPTIC FOAM Hand Soap ELIMINATES 99.999% OF MOST COMMON GERMS THAT CAUSES ILLNESS NO RINSE MOISTURIZES LEAVES SKIN SOFT 8.4 fl oz (250 ml)